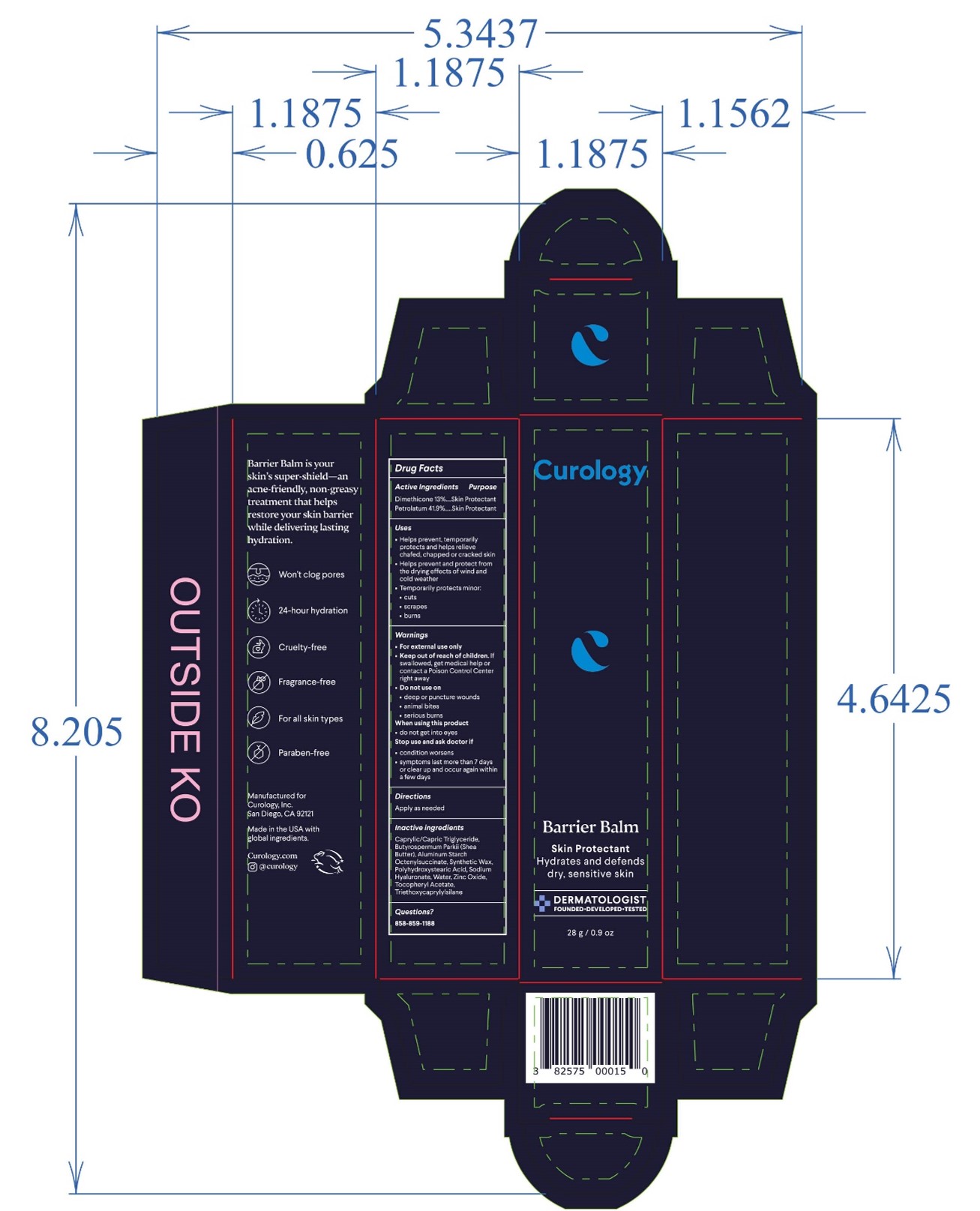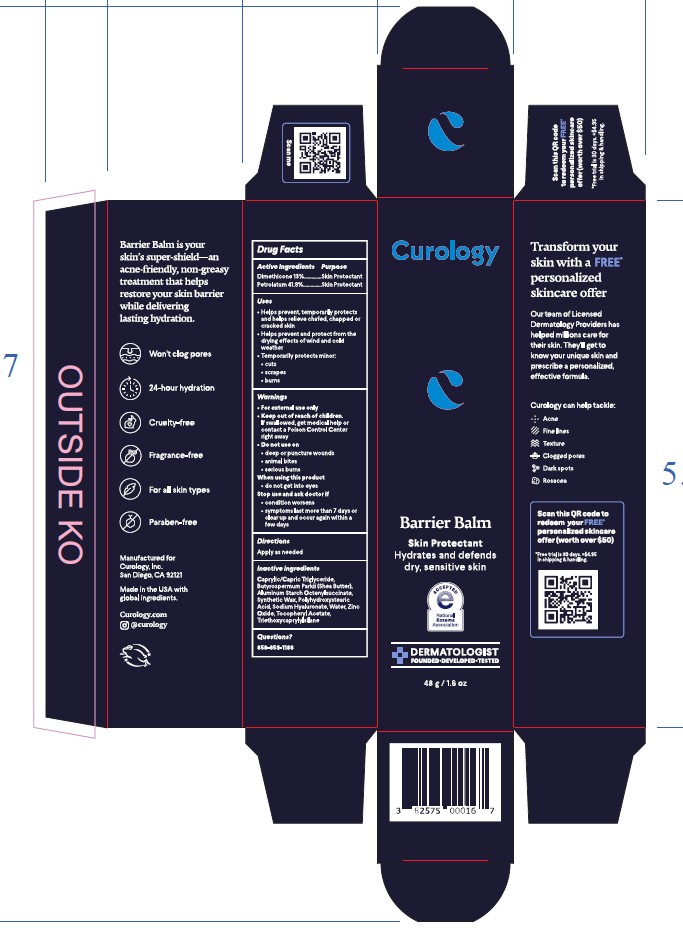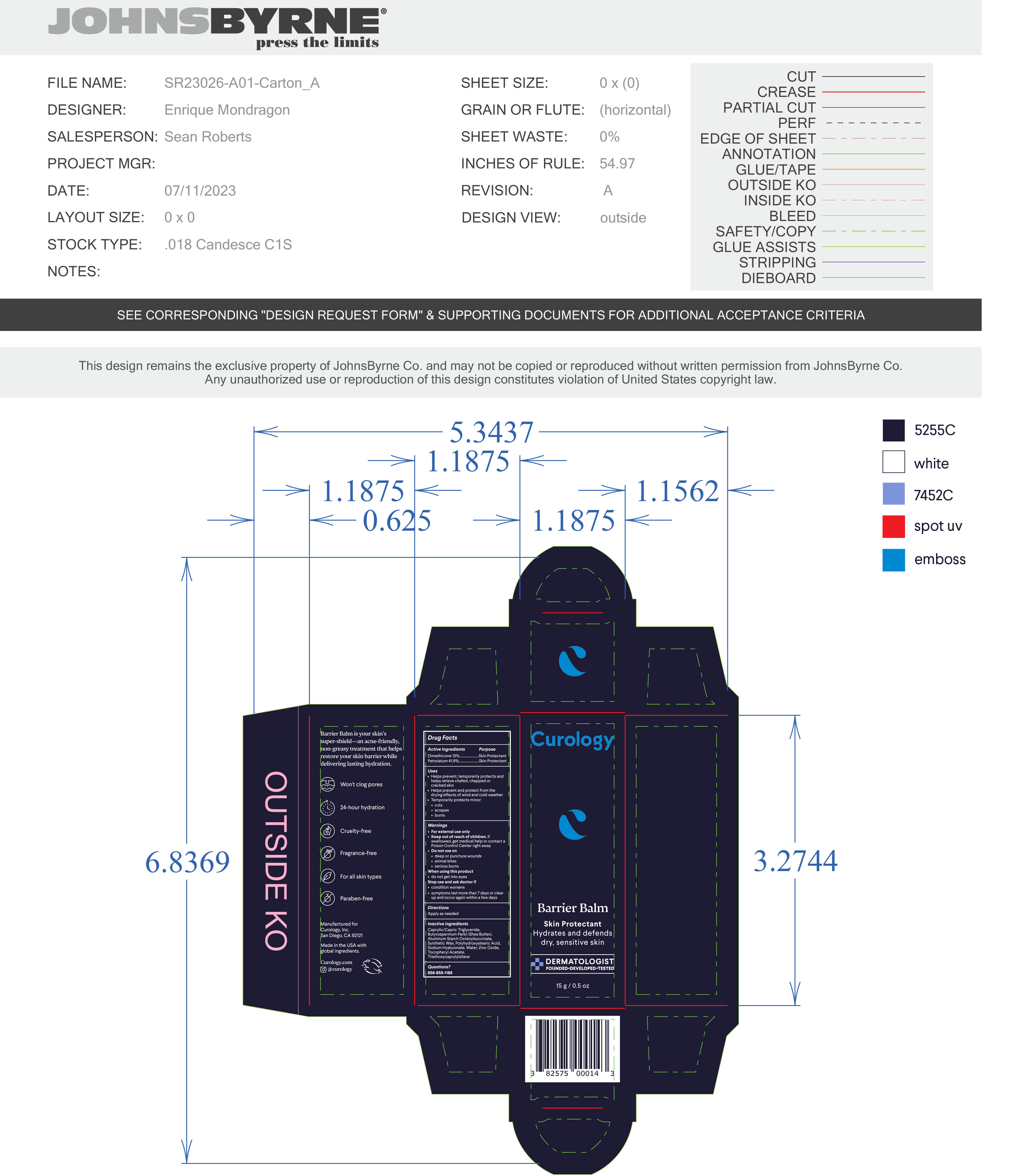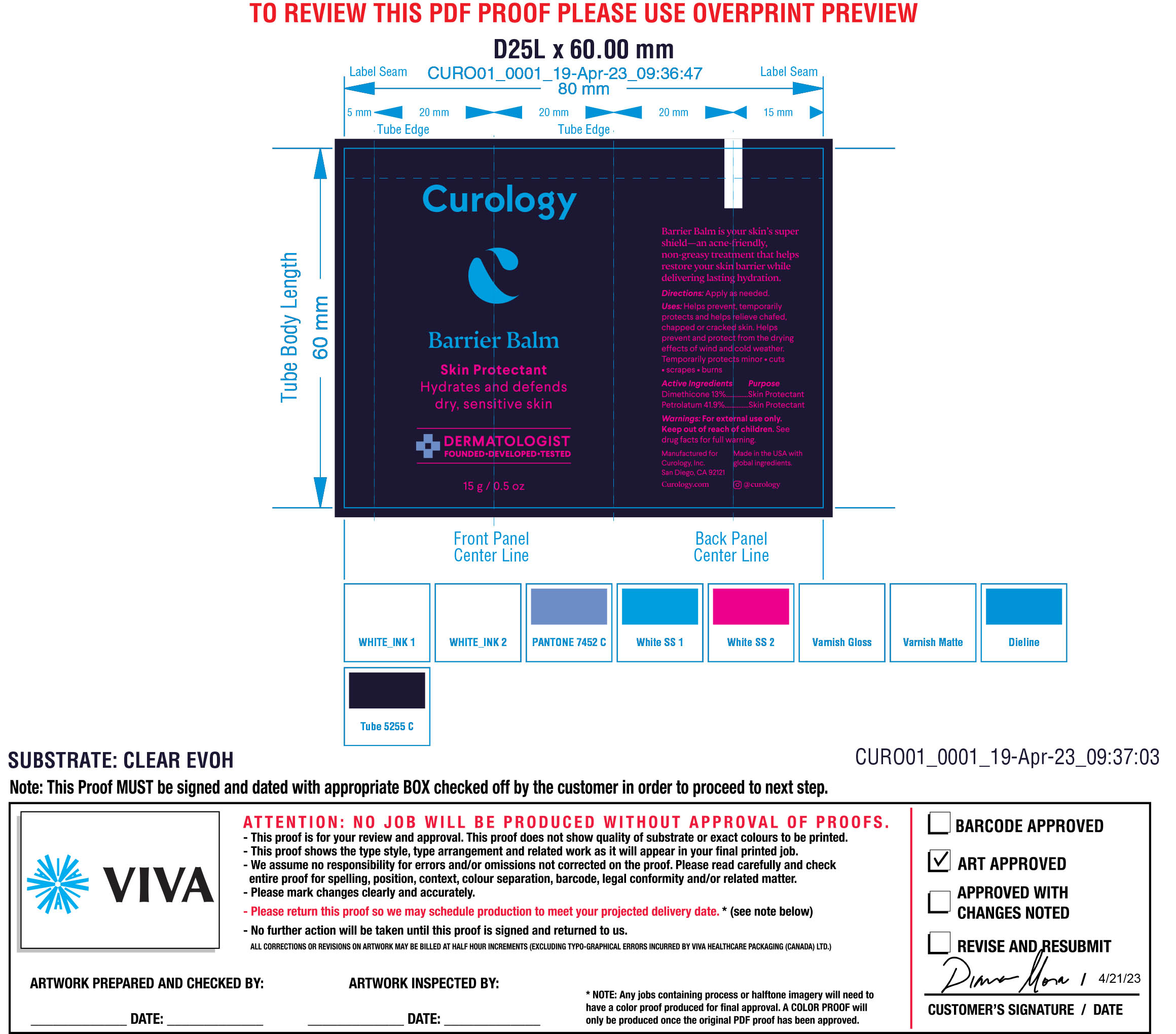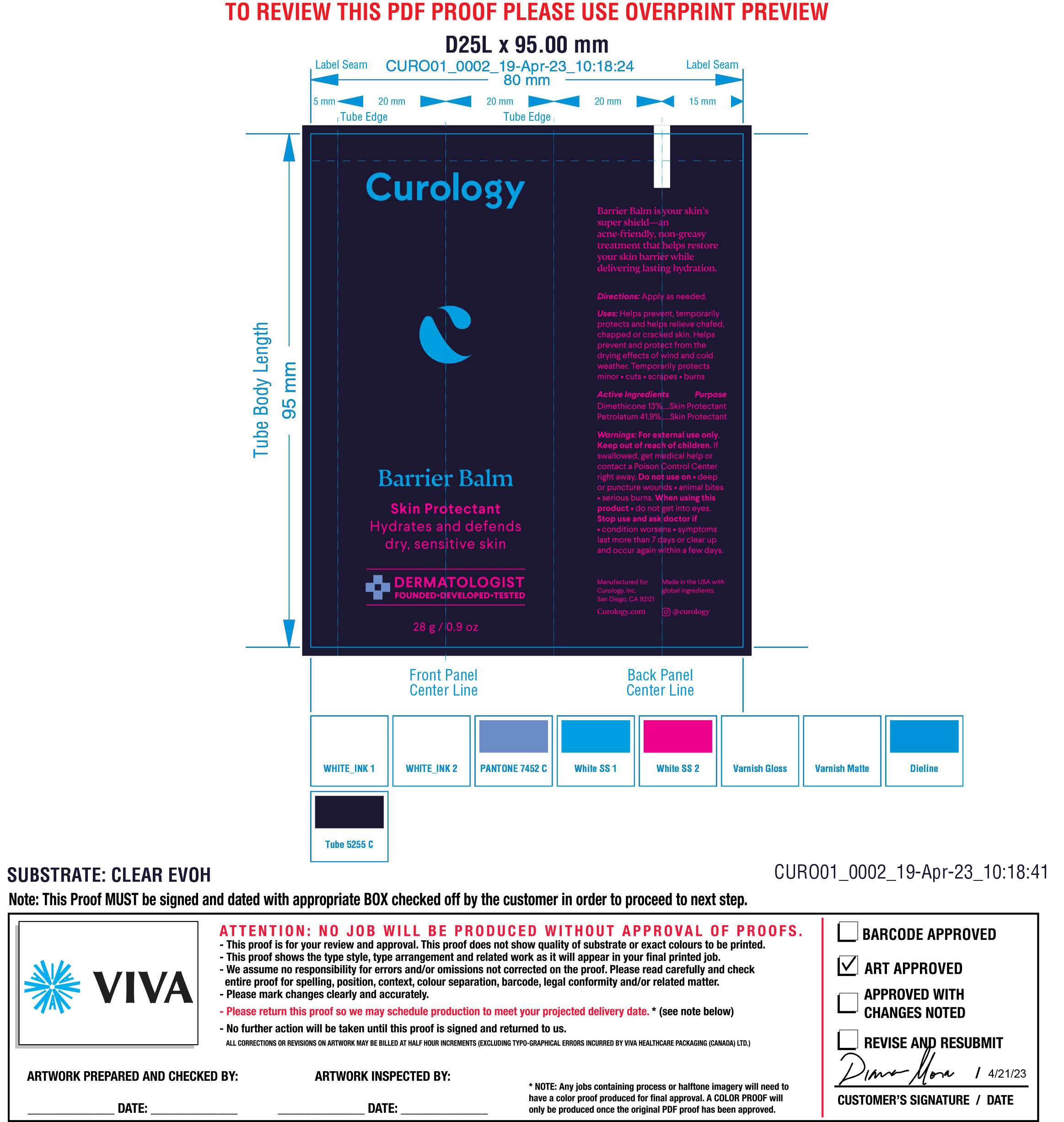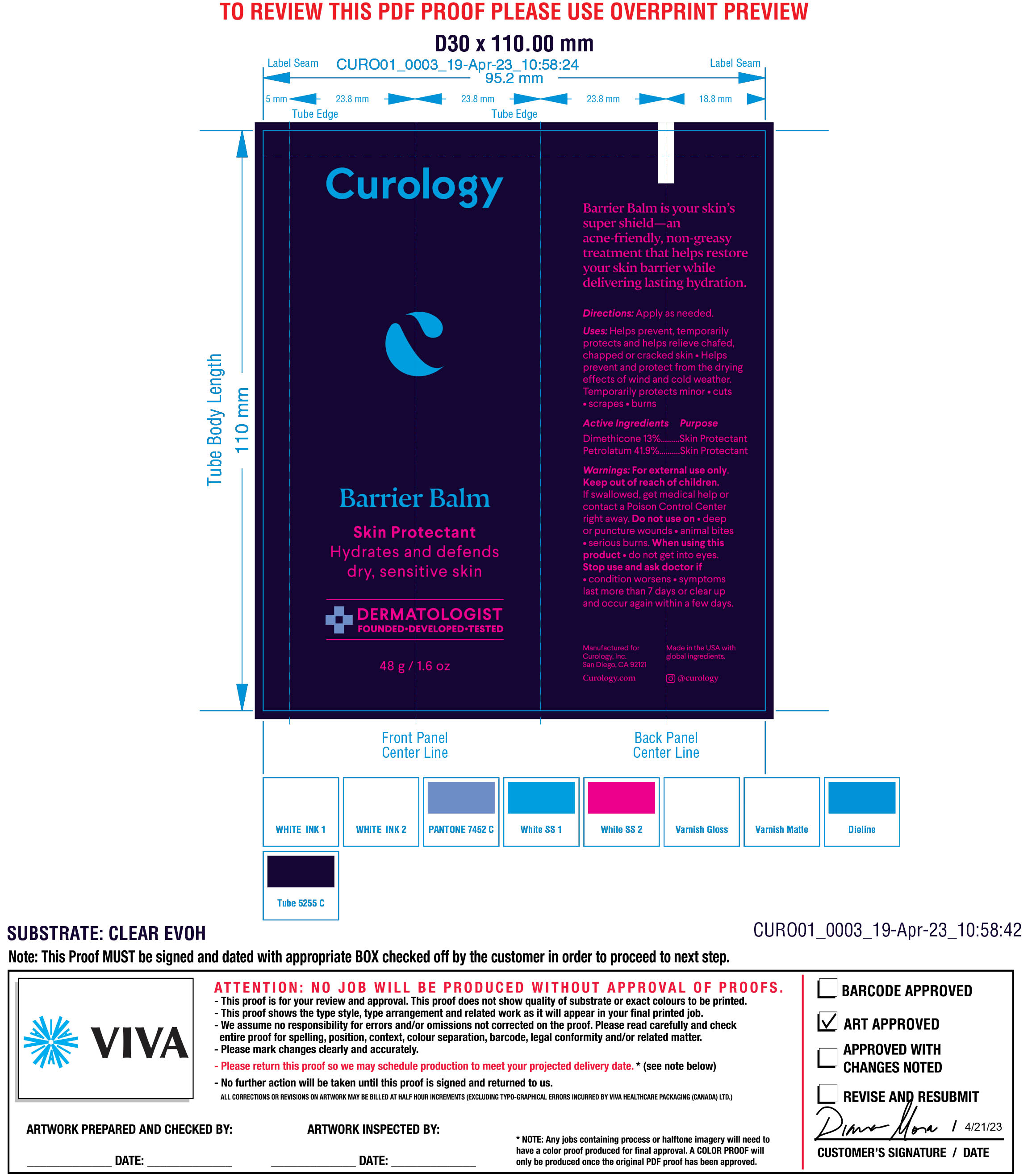 DRUG LABEL: Barrier Balm
NDC: 51514-0363 | Form: OINTMENT
Manufacturer: Autumn Harp, Inc.
Category: otc | Type: HUMAN OTC DRUG LABEL
Date: 20230801

ACTIVE INGREDIENTS: DIMETHICONE 20 13 g/100 g; PETROLATUM 41.9 g/100 g
INACTIVE INGREDIENTS: POLYHYDROXYSTEARIC ACID (2300 MW); ZINC OXIDE; .ALPHA.-TOCOPHEROL ACETATE, DL-; SYNTHETIC WAX (1800 MW); WATER; BUTYLATED HYDROXYTOLUENE; MEDIUM-CHAIN TRIGLYCERIDES; SHEA BUTTER; ALUMINUM STARCH OCTENYLSUCCINATE; TRIETHOXYCAPRYLYLSILANE; HYALURONATE SODIUM

Skin Barrier Balm

Active Ingredient

Petrolatum 41.9%

Dimethicone 13.0%

PURPOSE

Helps prevent, temporarily protects and helps relieve chafed, chapped or cracked skin

Helps prevent and protect from the drying effects of wind and cold weather

Temporarily protects minor cuts, scrapes, burns

Directions

Apply as needed

Warnings

For external use only

Keep out of reach of children. If swallowed, get medical help or contact a Poison Control Center right away

Do not use on deep or puncture wounds, animal bites, serious burns

When using this product do not get into eyes

Stop use and ask doctor if condition worsens, symptoms last more than 7 days or clear up and occur again within a few days

INACTIVE INGREDIENT

Caprylic/Capric triglyceride, Butyrospermum Parkii (Shea Butter), Aluminum Starch Octenylsuccinate, Synthetic Wax, Polyhydroxystearic Acid, Sodium Hyaluronate, Water, Zinc Oxide, Tocopheryl Acetate, Triethoxycaprylylsilane

Questions?

858-859-1188

Keep out of reach of children. If swallowed, get medical help or contact a Poison Control Center right away

DOSAGE AND ADMINISTRATION

Apply as needed